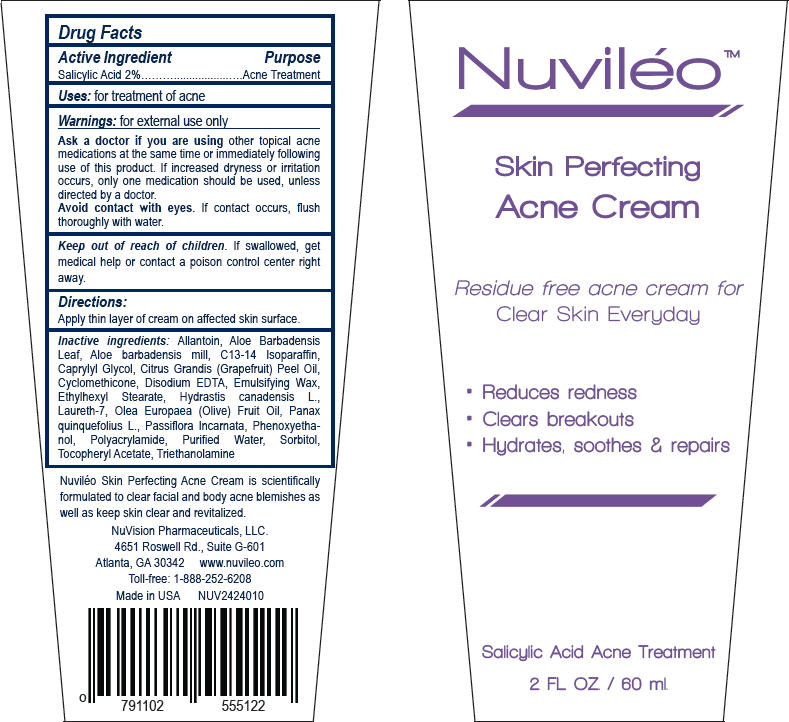 DRUG LABEL: Nuvileo Skin Perfecting Acne
NDC: 58133-500 | Form: CREAM
Manufacturer: Cosmetic Specialty Labs, Inc.
Category: otc | Type: HUMAN OTC DRUG LABEL
Date: 20150715

ACTIVE INGREDIENTS: Salicylic Acid 20 mg/1 mL
INACTIVE INGREDIENTS: Allantoin; Aloe Vera Leaf; Aloe Vera Whole; C13-14 Isoparaffin; Caprylyl Glycol; Citrus Maxima Fruit Rind Oil; Cyclomethicone; Edetate Disodium; Ethylhexyl Stearate; Hydrastis Canadensis Whole; Laureth-7; Olive Oil; Panax Quinquefolius Whole; Passiflora Incarnata Flowering Top; Phenoxyethanol; Water; Sorbitol; .Alpha.-Tocopherol Acetate; Trolamine

Nuviléo™ Skin Perfecting Acne Cream

Drug Facts

Active Ingredient

Salicylic Acid 2%

Purpose

Acne Treatment

Uses

for treatment of acne

Warnings

for external use only

Ask a doctor if you are using other topical acne medications at the same time or immediately following use of this product. If increased dryness or irritation occurs, only one medication should be used, unless directed by a doctor.

WHEN USING

Avoid contact with eyes. If contact occurs, flush thoroughly with water.

Keep out of reach of children. If swallowed, get medical help or contact a poison control center right away.

Directions

Apply thin layer of cream on affected skin surface.

Inactive ingredients

Allantoin, Aloe Barbadensis Leaf, Aloe barbadensis mill, C13-14 Isoparaffin, Caprylyl Glycol, Citrus Grandis (Grapefruit) Peel Oil, Cyclomethicone, Disodium EDTA, Emulsifying Wax, Ethylhexyl Stearate, Hydrastis canadensis L., Laureth-7, Olea Europaea (Olive) Fruit Oil, Panax quinquefolius L., Passiflora Incarnata, Phenoxyethanol, Polyacrylamide, Purified Water, Sorbitol, Tocopheryl Acetate, Triethanolamine

PRINCIPAL DISPLAY PANEL - 60 ml Tube Label

Nuviléo™

Skin Perfecting
Acne Cream

Residue free acne cream for
Clear Skin Everyday

- Reduces redness
- Clears breakouts
- Hydrates, soothes & repairs

Salicylic Acid Acne Treatment

2 FL. OZ. / 60 ml.